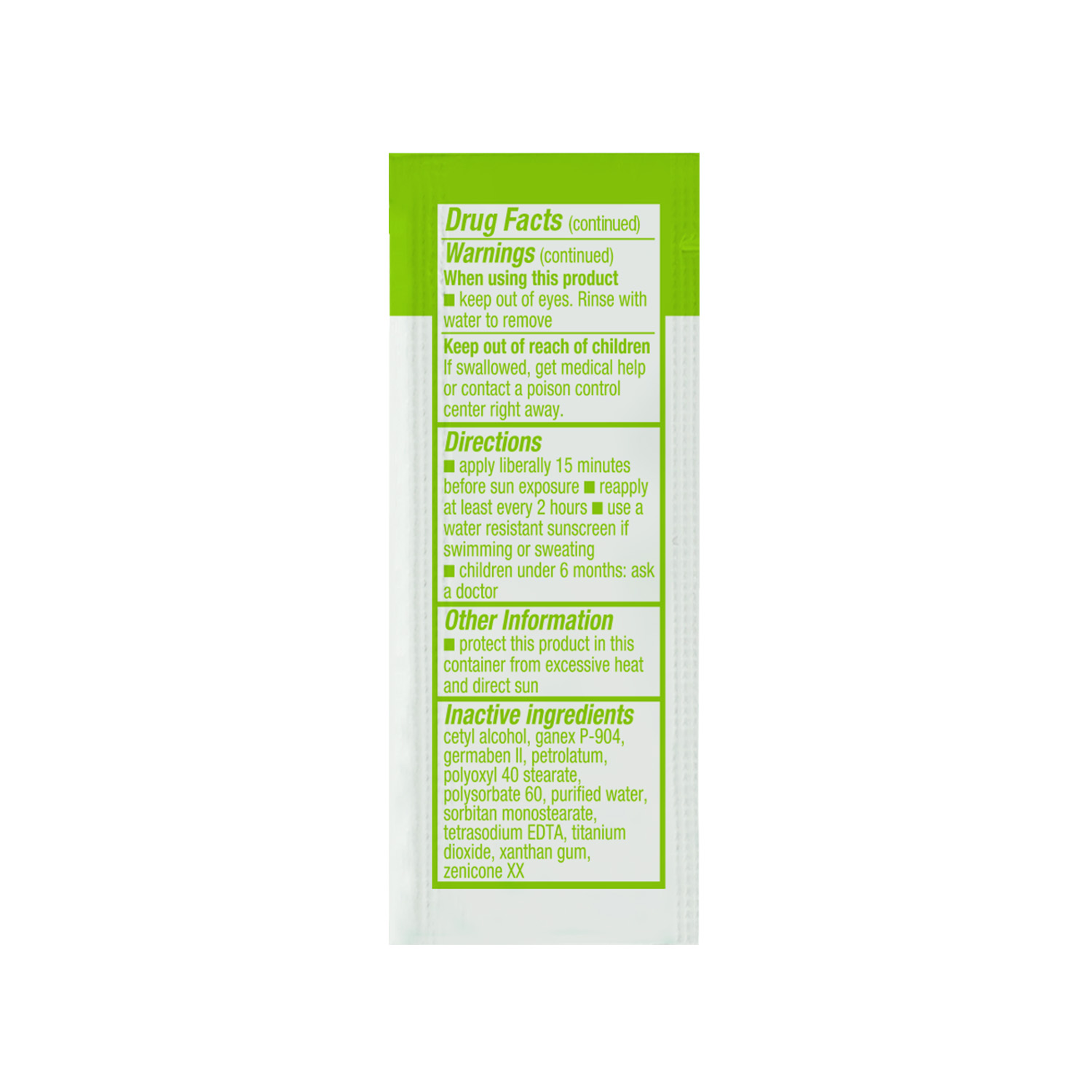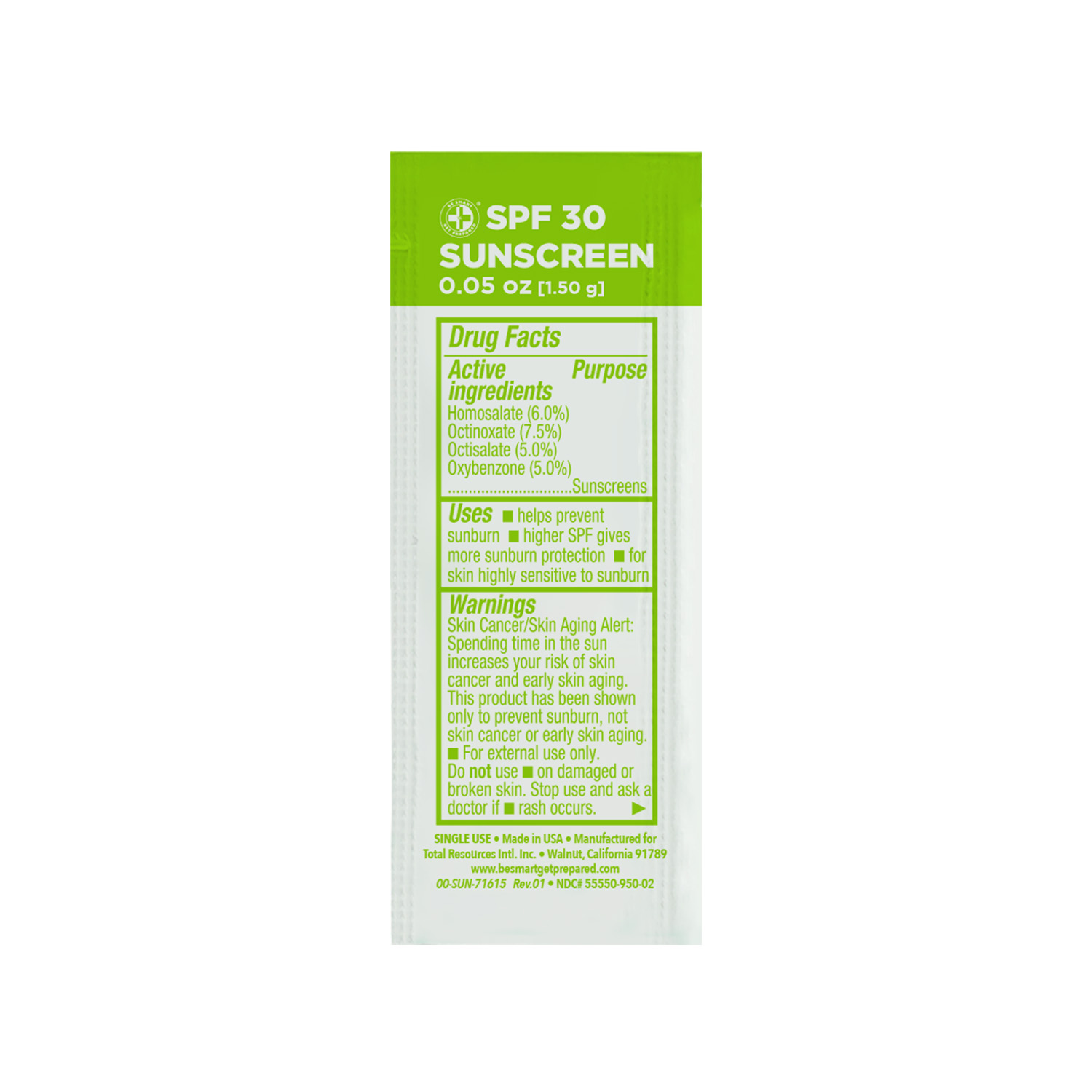 DRUG LABEL: Be Smart Get Prepared Sunscreen
NDC: 55550-950 | Form: OINTMENT
Manufacturer: Total Resources International Inc.
Category: otc | Type: HUMAN OTC DRUG LABEL
Date: 20221122

ACTIVE INGREDIENTS: OCTISALATE 5 mg/1 g; OXYBENZONE 5 mg/1 g; HOMOSALATE 6 mg/1 g; OCTINOXATE 7.5 mg/1 g
INACTIVE INGREDIENTS: POLYSORBATE 60; XANTHAN GUM; POVIDONE K30; DIMETHICONE; SORBITAN MONOSTEARATE; EDETATE SODIUM; CETYL ALCOHOL; WATER; TITANIUM DIOXIDE; DIAZOLIDINYL UREA; PETROLATUM; POLYOXYL 40 STEARATE

Be Smart Get Prepared Sunscreen

Active ingredient Purpose

Homosalate (6.0%)

Octinoxate (7.5%)

Octisalate (5.0%)

Oxybenzone (5.0%)....................Sunscreens

Uses

- helps prevent sunburn
- higher SPF gives more sunburn protection
- for skin highly sensitive to sunburn

WARNINGS

Skin cancer/skin aging alert: spending time in the sun increases your risk of skin cancer and early skin aging.This product has been shown only to prevent sunburn, not skin cancer or early aging skin.

For external use only.

Stop use and ask a doctor if

- rash occurs.

Do not use • on damaged or broken skin.

Stop use, ask a doctor if

- rash occurs

Keep out of reach of children

if swallowed, get medical help or contact a poison control center right away.

Directions

- apply liberally 15 minutes before sun exposure
- reapply at least every two hours
- use a water resistant sunscreen if swimming or sweating
- children under 6 months: ask a doctor

Other Information

- protect this product in this container from excessive heat and direct sun

Inactive ingredients

cetyl alcohol, ganex P-904, germaben II, petrolatum, polyoxyl 40 stearate, polysorbate 60, purified water, sorbitan monostearate, tetrasodium EDTA, titanium dioxide, xanthan gum, zenicone XX